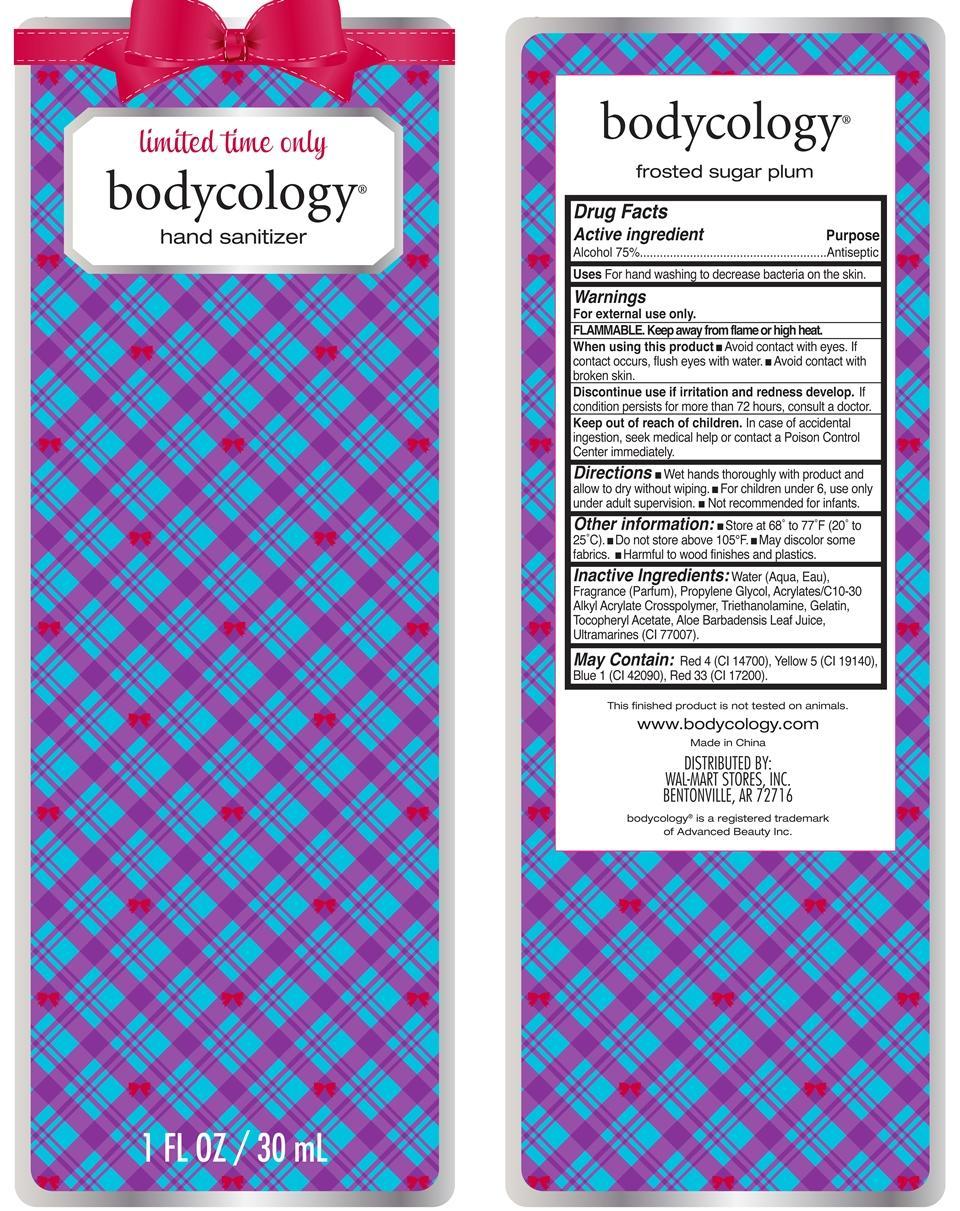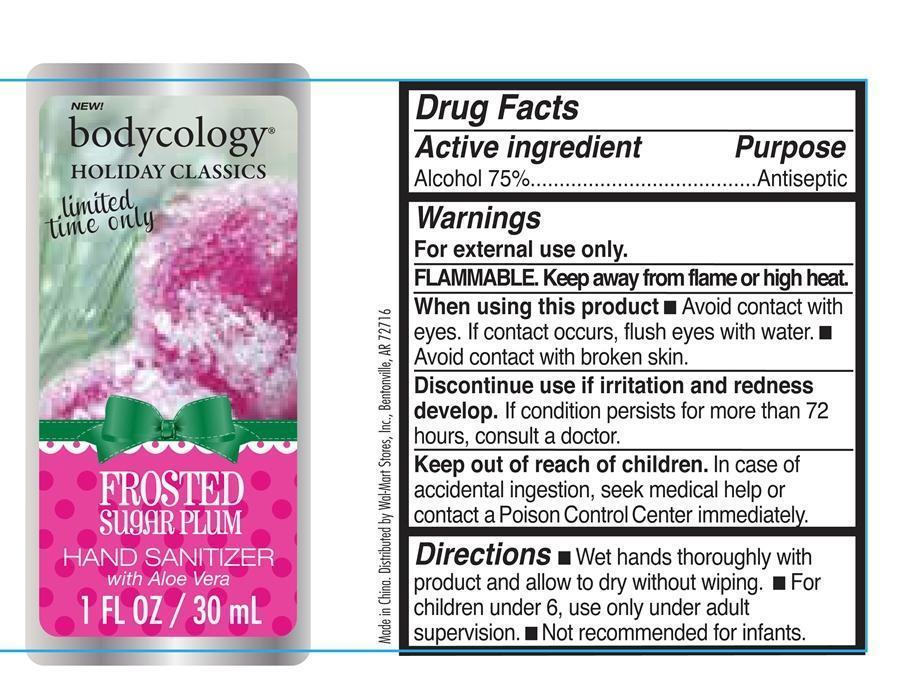 DRUG LABEL: frosted sugar plum hand sanitizer
NDC: 49035-113 | Form: LIQUID
Manufacturer: Wal-Mart Stores Inc
Category: otc | Type: HUMAN OTC DRUG LABEL
Date: 20130529

ACTIVE INGREDIENTS: ALCOHOL 75 g/100 mL
INACTIVE INGREDIENTS: WATER; CARBOMER COPOLYMER TYPE A (ALLYL PENTAERYTHRITOL CROSSLINKED); TROLAMINE; PROPYLENE GLYCOL; GELATIN; .ALPHA.-TOCOPHEROL ACETATE; ALOE VERA LEAF; ULTRAMARINE BLUE; FD&C RED NO. 4; FD&C YELLOW NO. 5; FD&C BLUE NO. 1; D&C RED NO. 33

frosted sugar plum hand sanitizer

Active ingredient Purpose

Alcohol 75% Antiseptic

PURPOSE

Uses For hand washing to decrease bacteria on the skin.

Keep out of reach of children. In case of accidental ingestion, seek professional assistance or contact a Poison Control Center immediately.

INDICATIONS AND USAGE

Discontinue use if irritation and redness develop. If condition persists for more than 72 hours, consult a doctor.

Warnings

For external use only.

FLAMMABLE. Keep away from flame or high heat.

When using this product

Avoid contact with eyes. If contact occurs, flush eyes with water.

Avoid contact with broken skin

Directions

Wet hands thoroughly with product and allow to dry without wiping.

For children under 6, use only under adult supervision.

Not recommended for infants.

INACTIVE INGREDIENT

Inactive ingredients: Water (Aqua, Eau), Fragrance (Parfum), Propylene Glycol, Acrylates/C10-30 Alkyl Acrylate Crosspolymer, Triehanolamine, Gelatin, Tocopheryl Acetate, Aloe Barbadensis Leaf Juice, Ultramarines (CI 77007).

May Contain: FD&C Red No. 4 (CI 14700), FD&C Yellow No. 5 (CI 19140), FD&C Blue No. 1 (CI 42090), D&C Red No. 33 (CI 17200).

PACKAGE LABEL

limited time only

bodycology hand sanitizer frosted sugar plum

1 Fl Oz/ 30 mL